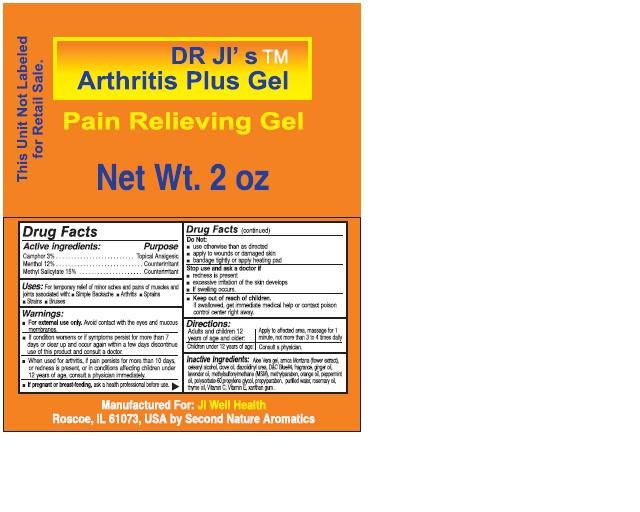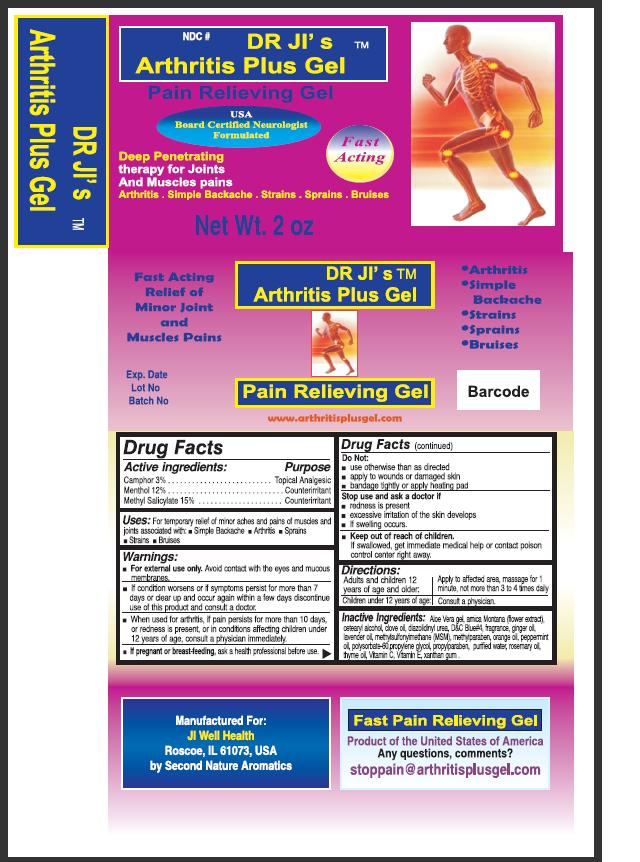 DRUG LABEL: Dr. JIs Arthritis Plus
NDC: 50810-1000 | Form: GEL
Manufacturer: JI Well Health Company
Category: otc | Type: HUMAN OTC DRUG LABEL
Date: 20100511

ACTIVE INGREDIENTS: CAMPHOR (NATURAL) 3 mg/100 mg; MENTHOL 12 mg/100 mg; METHYL SALICYLATE 15 mg/100 mg
INACTIVE INGREDIENTS: ALOE VERA LEAF; ARNICA MONTANA; CETOSTEARYL ALCOHOL; CLOVE OIL; GINGER OIL; LAVENDER OIL; DIMETHYL SULFONE; METHYLPARABEN; ORANGE OIL; PEPPERMINT OIL; POLYSORBATE 60; PROPYLENE GLYCOL; PROPYLPARABEN; WATER; ROSEMARY OIL; THYME OIL; ASCORBIC ACID; ALPHA-TOCOPHEROL; XANTHAN GUM

Dr. JI's Arthritis Plus Gel

Drug Facts

Active Ingredients Purpose

Camphor 3%........................................Topical Analgesics

Menthol 12%.....................................Counter Irritant

Methyl Salicylate............................Counter Irritant

USES

For temporary relief of minor aches and pains of muscles and joints associated with: simple backache, arthritis, sprains, strains, bruises

WARNINGS:

For external Use only. Avoid contact with the eyes and mucous membranes.

STOP USE

If condition worsens or if symptoms persist for more than 7 days or clear up and occur again within a few days, discontinue use of this product and consult a doctor.

ASK DOCTOR

When used for arthritis, if pain persists for more than 10 days, or redness is present, or in conditions affecting children under 12 years of age, consult a physician immediately.

PREGNANCY OR BREAST FEEDING

If pregnant or breast-feeding, ask a health professional before use.

Do not:

use otherwise than as directed

apply to wounds or damaged skin

bandage tightly or apply heating pad

Stop use and ask a doctor if

redness is present

excessive irritation of the skin develops

if swelling occurs

DIRECTIONS:

Adults and children 12 years of age and older: Apply to affected area, massage for 1 minute, not more than 3 to 4 times daily

Children under 12 years of age: Consult a physician.

INACTIVE INGREDIENT

Aloe Vera gel, arnica Montana (flower extract, cetearyl alcohol, clove oil, diazolidinyl urea, DandC Blue 4, fragrance, ginger oil, lavender oil, methylsulfonylmethane (MSM), methylparaben, orange oil, peppermint oil, polysorbate-60, propylene glycol, propylparaben, purified water, rosemary oil, thyme oil, Vitamin C, Vitamin E, xanthan gum.

QUESTIONS

Fast Pain Relieving Gel

Product of the United States of America

Any questions, comments?

stoppain@arthritisplusgel.com

DESCRIPTION

Manufactured for:

JI Well Health

Roscoe, IL 61073, USA

by Second Nature Aromatics

PACKAGE LABEL

Dr. JI's Arthrits Plus Gel

Pain Relieving Gel

USA Board Certified Neurologist Formulated

Deep penetrating therapy for joints and muscles pain Fast Acting

Arthritis Simple Backache Strains Sprains Bruises

Net Weight 2oz.

Fast Acting Relief of Minor Joint and Muscles Pains

Dr. JI's (TM) Arthritis Plus Gel

Pain Relieving Gel

Arthritis

Simple Backache

Strains

Sprains

Bruises

Exp. Date

Lot No.

Batch No.

Pain Relieving Gel

www.arthritisplusgel.com